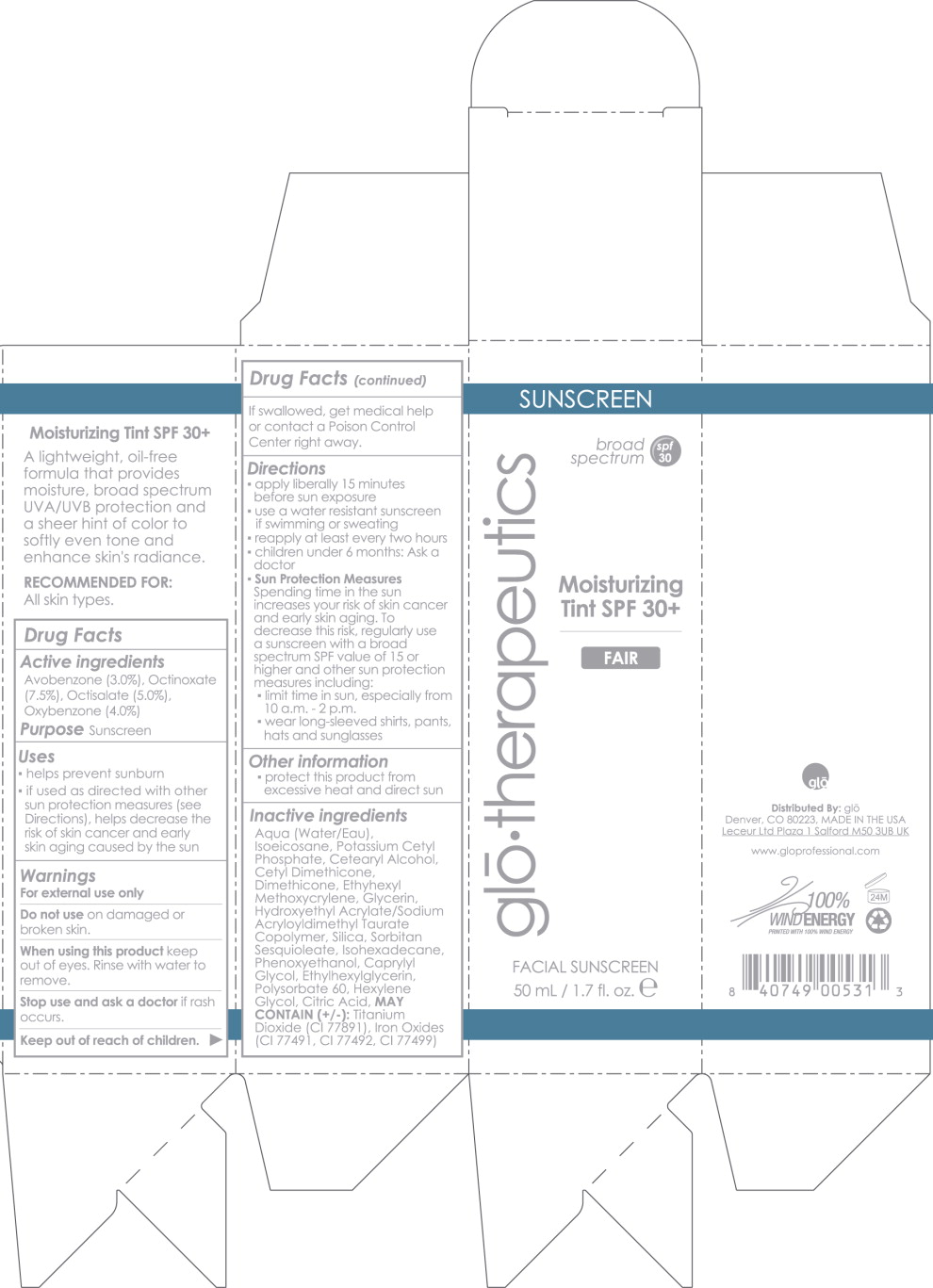 DRUG LABEL: Moisturizing Tint 
NDC: 60541-0706 | Form: LOTION
Manufacturer: Hayden Caleel LLC
Category: otc | Type: HUMAN OTC DRUG LABEL
Date: 20140301

ACTIVE INGREDIENTS: Octinoxate 7.5 g/1 mL; Octisalate 5 g/1 mL; Oxybenzone 4 g/1 mL; Avobenzone 3 g/1 mL
INACTIVE INGREDIENTS: Water; Isoeicosane; Potassium Cetyl Phosphate; Cetostearyl Alcohol; Cetyl Dimethicone 45; Dimethicone; Ethylhexyl Methoxycrylene; Glycerin; Hydroxyethyl Acrylate/Sodium Acryloyldimethyl Taurate Copolymer (45000 Mpa.S At 1%); Silicon Dioxide; Sorbitan Sesquioleate; Isohexadecane; Phenoxyethanol; Caprylyl Glycol; Ethylhexylglycerin; Polysorbate 60; Hexylene Glycol; Citric Acid Monohydrate; Titanium Dioxide; Ferric Oxide Red

Drug Facts

Active Ingredients:

Avobenzone (3.0%)

Octinoxate (7.5%)

Octisalate (5.0%)

Oxybenzone (4.0%)

Purpose:

Sunscreen

Uses

- helps prevent sunburn
- if used as directed with other sun protection measures (see Directions), helps decrease the risk of skin cancer and early skin aging caused by the sun

Warnings

For external use only

Do not use on damaged or broken skin.

When using this product keep out of the eyes. Rinse with water to remove.

Stop use and ask a doctor if skin rash occurs.

Keep out of reach of children. If swallowed, get medical help or contact a Poison Control Center right away.

Directions

- apply liberally 15 minutes before sun exposure
- use a water resistant sunscreen if swimming or sweating
- reapply at least every 2 hours
- Children under 6 months of age: Ask a doctor
- Sun Protection Measures
  Spending time in the sun increases your risk of skin cancer and early skin aging. To decrease this risk, regularly use a sunscreen with a broad spectrum SPF value of 15 or higher and other sun protection measures including:
  - limit time in the sun, especially from 10 a.m. – 2 p.m.
  - wear long-sleeved shirts, pants, hats, and sunglasses

Other information

- protect the product in this container from excessive heat and direct sun

Inactive ingredients

Aqua (Water/Eau)

Isoeicosane

Potassium Cetyl Phosphate

Cetearyl Alcohol

Cetyl Dimethicone

Dimethicone

Ethyhexyl Methoxycrylene

Glycerin

Hydroxyethyl Acrylate/Sodium Acryloyldimethyl Taurate Copolymer

Silica

Sorbitan Sesquioleate

Isohexadecane

Phenoxyethanol

Caprylyl Glycol

Ethylhexylglycerin

Polysorbate 60

Hexylene Glycol

Citric Acid

MAY CONTAIN (+/-):

Titanium Dioxide (CI 77891)

Iron Oxides (CI 77491, CI 77492, CI 77499)

Principal Display Panel - 50mL Carton Label

SUNSCREEN

broad
spectrum
spf 30

glo·therapeutics

Moisturizing
Tint SPF 30+

FAIR

FACIAL SUNSCREEN

50 mL / 1.7 fl. oz. e